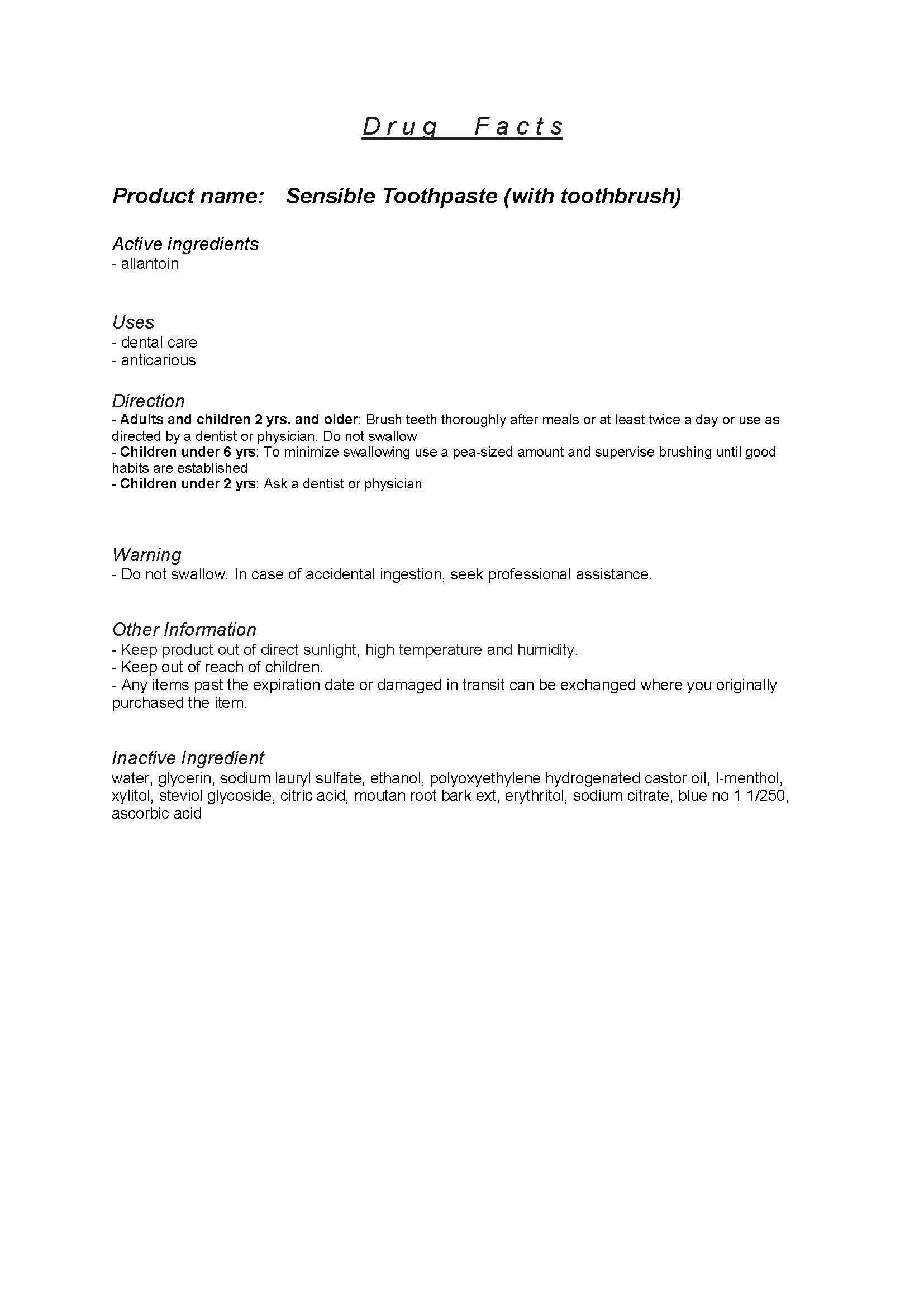 DRUG LABEL: Sensible
                
NDC: 69086-1001 | Form: PASTE
Manufacturer: Guardian Angel of Preventive Dentistry
Category: otc | Type: HUMAN OTC DRUG LABEL
Date: 20140711

ACTIVE INGREDIENTS: SODIUM LAURYL SULFATE 2 g/100 g
INACTIVE INGREDIENTS: ALLANTOIN; GLYCERIN; LEVOMENTHOL

Drug Facts

ACTIVE INGREDIENT

sodium lauryl sulfate

INACTIVE INGREDIENT

water, glycerin, allantoin, ethanol, polyoxyethylene hydrogenated castor oil, l-menthol, xylitol, steviol glycoside, citric acid, moutan root bark ext, erythritol, sodium citrate, blue no 1 1/250, ascorbic acid

PURPOSE

dental care

keep out of reach of the children

INDICATIONS AND USAGE

- Adults and children 2 yrs. and older: Brush teeth thoroughly after meals or at least twice a day or use as directed by a dentist or physician. Do not swallow
- Children under 6 yrs: To minimize swallowing use a pea-sized amount and supervise brushing until good habits are established
- Children under 2 yrs: Ask a dentist or physician

WARNINGS

do not swallow

DOSAGE AND ADMINISTRATION

dental care only